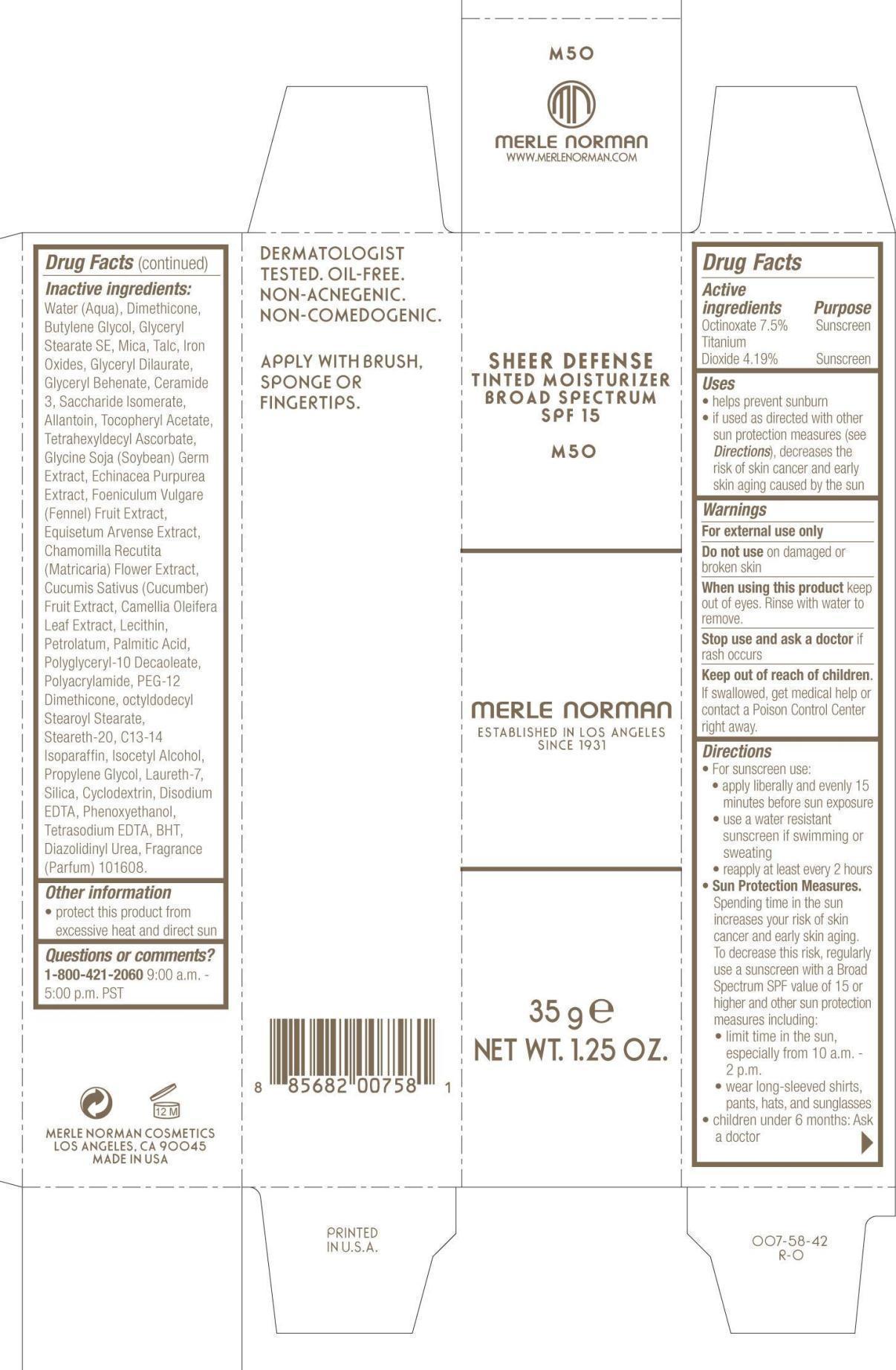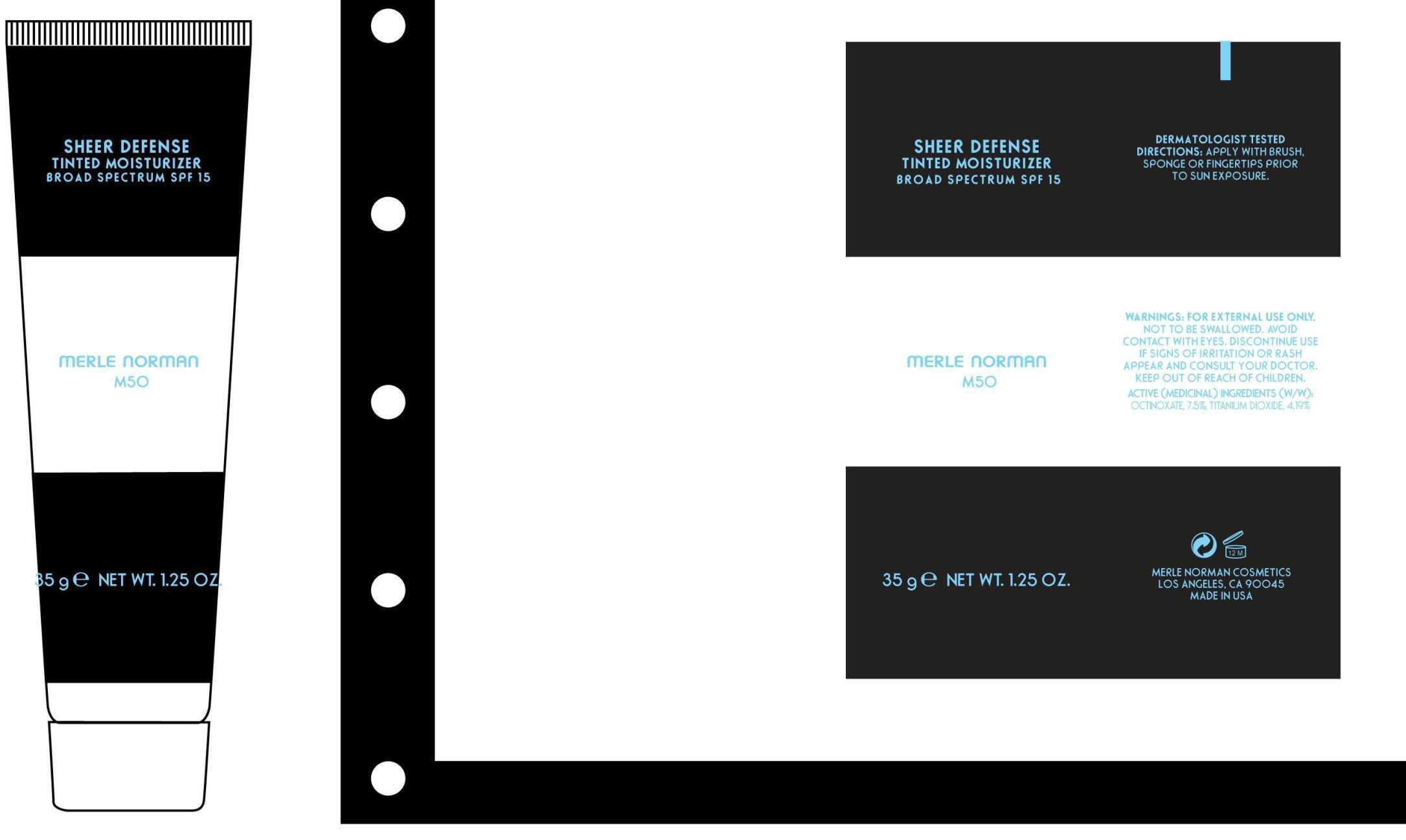 DRUG LABEL: Sheer Defense Tinted Moisturizer Broad Spectrum SPF 15 M50
NDC: 57627-153 | Form: LIQUID
Manufacturer: Merle Norman Cosmetics, Inc.
Category: otc | Type: HUMAN OTC DRUG LABEL
Date: 20251119

ACTIVE INGREDIENTS: OCTINOXATE 7.5 g/100 g; TITANIUM DIOXIDE 4.19 g/100 g
INACTIVE INGREDIENTS: WATER; DIMETHICONE; BUTYLENE GLYCOL; GLYCERYL STEARATE SE; MICA; TALC; FERRIC OXIDE RED; FERRIC OXIDE YELLOW; FERROSOFERRIC OXIDE; GLYCERYL DILAURATE; GLYCERYL MONOBEHENATE; CERAMIDE 3; SACCHARIDE ISOMERATE; ALLANTOIN; .ALPHA.-TOCOPHEROL ACETATE; TETRAHEXYLDECYL ASCORBATE; SOYBEAN GERM; ECHINACEA PURPUREA; FENNEL SEED; EQUISETUM ARVENSE BRANCH; CHAMOMILE; CUCUMBER; CAMELLIA OLEIFERA LEAF; LECITHIN, SOYBEAN; PETROLATUM; PALMITIC ACID; POLYACRYLAMIDE (1500 MW); PEG-12 DIMETHICONE (300 CST); OCTYLDODECYL STEAROYL STEARATE; STEARETH-20; C13-14 ISOPARAFFIN; ISOCETYL ALCOHOL; PROPYLENE GLYCOL; LAURETH-7; SILICON DIOXIDE; EDETATE DISODIUM; PHENOXYETHANOL; EDETATE SODIUM; BUTYLATED HYDROXYTOLUENE; DIAZOLIDINYL UREA

Sheer Defense Tinted Moisturizer Broad Spectrum SPF 15 M50

Active Ingredients Purpose

Octinoxate7.5% Sunscreen

Titanium Dioxide 4.19% sunscreen

Uses

helps prevent sunburn

if used as directed with other sun protection measures (see Directions), decreases the risk of skin cancer and early skin aging caused by the sun.

Keep out of reach of children. If swallowed, get medical help or contact a Poison Control Center right away.

Stop use and ask a doctor if rash occurs

Warnings

For external use only

Do not use on damaged or broken skin

When using this product keep out of eyes. Rinse with water to remove.

Directions

For sunscreen use

apply liberally and evenly 15 minutes before sun exposure

use a water resistant sunscreen if swimming or sweating

reapply at least every 2 hours

Sun Protection Measures.

Spending time in the sun increases your risk of skin cancer and early skin aging. To decrease this risk, regularly use a sunscreen with a Broad Spectrum SPF value of 15 or higher and other sun protection measures including:

limiting time in the sun, especially from 10 a.m. - 2p.m.

wear long-sleeved shirts, pants, hats, and sunglasses

children under 6 months: ask a doctor

Inactive ingredients:

Water (Aqua), Dimethicone, Butylene Glycol, Glyceryl Stearate SE, Mica, Talc, Iron Oxides, Glyceryl Dilaurate, Glyceryl Behenate, Ceramide 3, Saccharide Isomerate, Allantoin, Tocopheryl Acetate, Tetrahexyldecyl Ascorbate, Glycine Soja (Soybean) Germ Extract, Echinacea Purpurea Extract, Foeniculum Vulgare (Fennel) Fruit Extract, Equisetum Arvense Extract, Chamomilla Recutita (Matricaria) Flower Extract, Cucumis Sativus (Cucumber) Fruit Extract, Camellia Oleifera Leaf Extract, Lecithin, Petrolatum, Palmitic Acid, Polyglyceryl-10 Decaoleate, Polyacrylamide, PEG-12 Dimethicone, octyldodecyl Stearoyl Stearate, Steareth-20, C13-14 Isoparaffin, Isocetyl Alcohol, Propylene Glycol, Laureth-7, Silica, Cyclodextrin, Disodium EDTA, Phenoxyethanol, Tetrasodium EDTA, BHT, Diazolidinyl Urea, Fragrance (Parfum)

PACKAGE LABEL

Sheer Defense Tinted Moisturizer Broad Spectrum SPF 15

M50

Merle Norman

Established in Los Angeles since 1931

35 g Net Wt. 1.25 Oz.